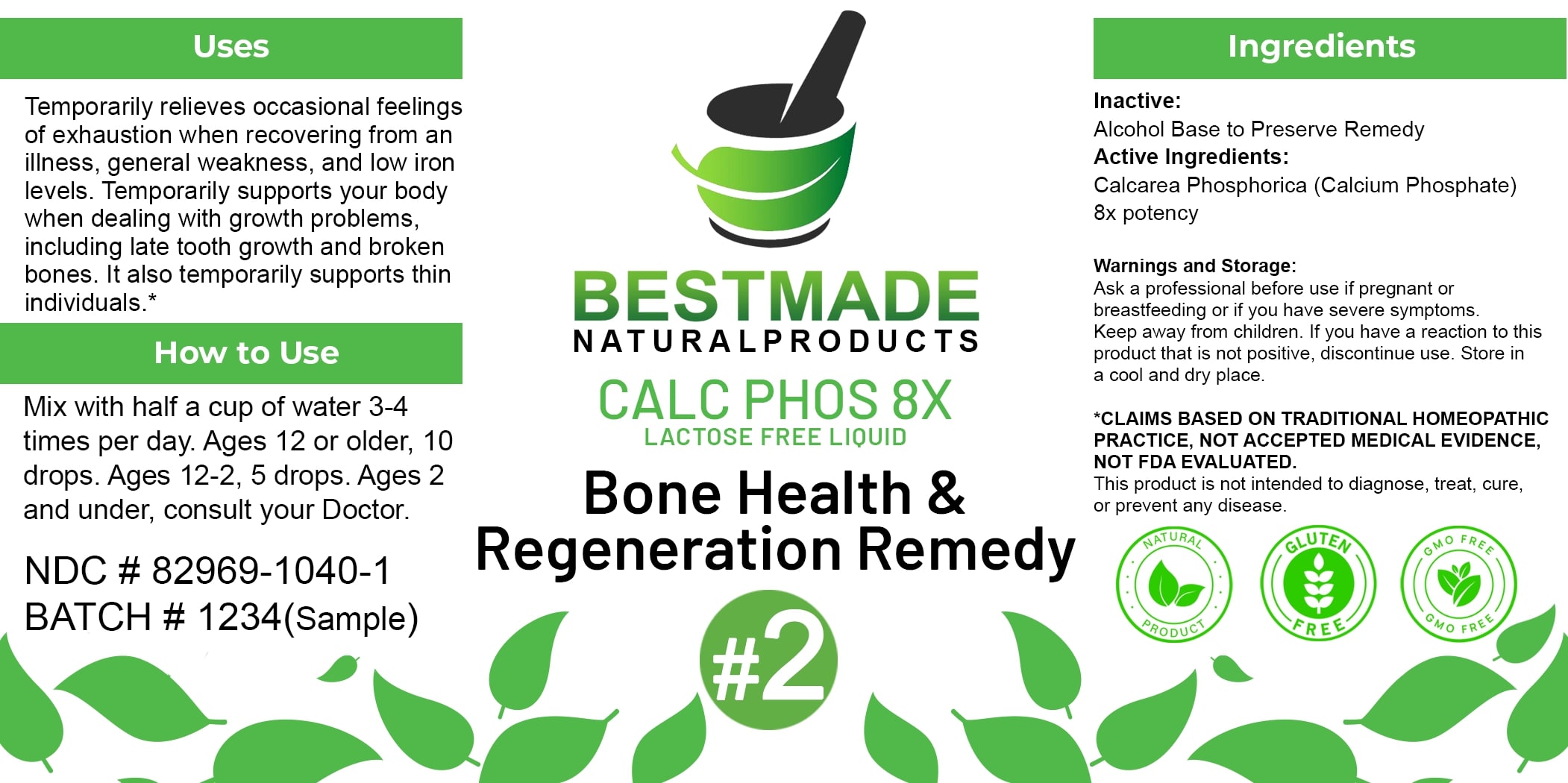 DRUG LABEL: Bestmade Natural Products Calc Phos 8x
NDC: 82969-1040 | Form: LIQUID
Manufacturer: Bestmade Natural Products
Category: homeopathic | Type: HUMAN OTC DRUG LABEL
Date: 20250403

ACTIVE INGREDIENTS: TRIBASIC CALCIUM PHOSPHATE 8 [hp_X]/8 [hp_X]
INACTIVE INGREDIENTS: ALCOHOL 8 [hp_X]/8 [hp_X]

Calc Phos 8x - liquid lactose free

DOSAGE AND ADMINISTRATION

How to Use

Mix with half a cup of water 3-4 times per day. Ages 12 or older, 10 drops. Ages 12-2, 5 drops. Ages 2 and under, consult your Doctor.

Uses

Temporarily relieves occasional feelings of exhaustion when recovering from an illness, general weakness, and low iron levels. Temporarily supports your body when dealing with growth problems, including late tooth growth and broken bones. It also temporarily supports thin individuals.*

*CLAIMS BASED ON TRADITIONAL HOMEOPATHIC PRACTICE, NOT ACCEPTED MEDICAL EVIDENCE. NOT FDA EVALUATED.

This product is not intended to diagnose, treat, cure, or prevent any disease.

Inactive:

Alcohol Base to Preserve Product

Active Ingredients:
Calcarea Phosphorica (Calcium Phosphate) 8x potency

Uses

Temporarily relieves occasional feelings of exhaustion when recovering from an illness, general weakness, and low iron levels. Temporarily supports your body when dealing with growth problems, including late tooth growth and broken bones. It also temporarily supports thin individuals.*

*CLAIMS BASED ON TRADITIONAL HOMEOPATHIC PRACTICE, NOT ACCEPTED MEDICAL EVIDENCE. NOT FDA EVALUATED.

This product is not intended to diagnose, treat, cure, or prevent any disease.

KEEP OUT OF REACH OF CHILDREN

Warnings and Storage:

Ask a professional before use if pregnant or breastfeeding or if you have severe symptoms. Keep away from children. If you have a reaction to this product that is not positive, discontinue use. Store in a cool and dry place.

Warnings and Storage:

Ask a professional before use if pregnant or breastfeeding or if you have severe symptoms. Keep away from children. If you have a reaction to this product that is not positive, discontinue use. Store in a cool and dry place.

*CLAIMS BASED ON TRADITIONAL HOMEOPATHIC PRACTICE, NOT ACCEPTED MEDICAL EVIDENCE. NOT FDA EVALUATED.

This product is not intended to diagnose, treat, cure, or prevent any disease.

Entire package label